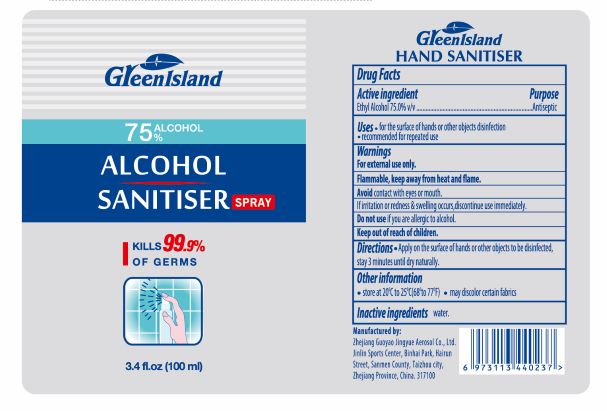 DRUG LABEL: Green Island Sanitiser
NDC: 75742-003 | Form: SPRAY
Manufacturer: Zhejiang Guoyao Aerosol Co., Ltd
Category: otc | Type: HUMAN OTC DRUG LABEL
Date: 20260105

ACTIVE INGREDIENTS: ALCOHOL 75 mL/100 mL
INACTIVE INGREDIENTS: WATER

Green Island Sanitiser

Active Ingredient(s)

Ethyl Alcohol 75% v/v.

Purpose

Antiseptic

Use

- for the surface of hands or other objects disinfection
- recommended for repeated use

Warnings

For external use only. Flammable. Keep away from heat or flame Avoid contact with eye or mouth. If irration or redness & swelling occurs, discontinue use immediately.

Do not use if you are allergic to alcohol

Keep out of reach of children.

Directions

- Apply on the surface of hands or other objects to be disinfected, stay 3 minutes until dry naturally

Other information

- Store at 20c to 25C (68F to 77F)
- may discolor certian fabrics

Inactive ingredients

water